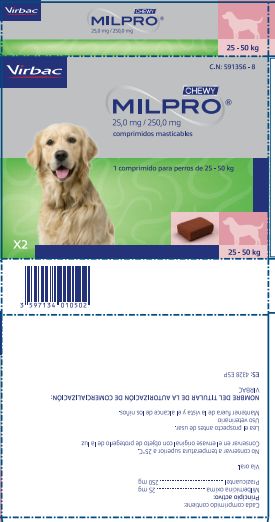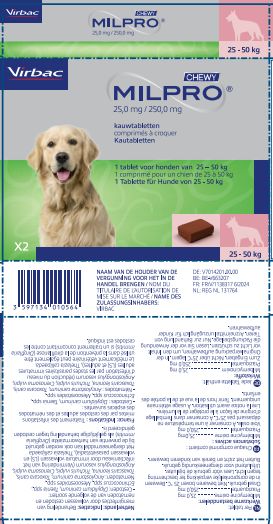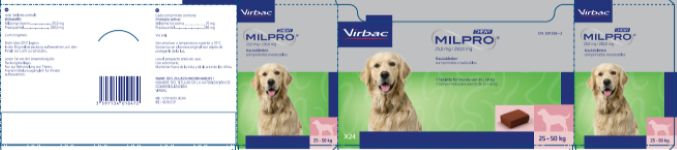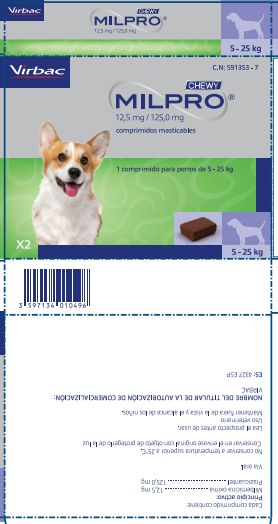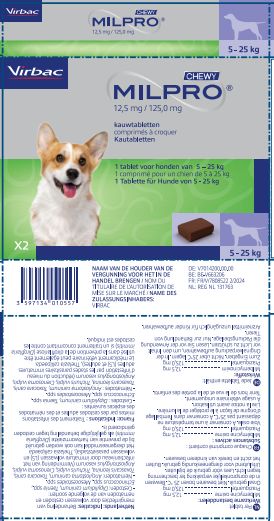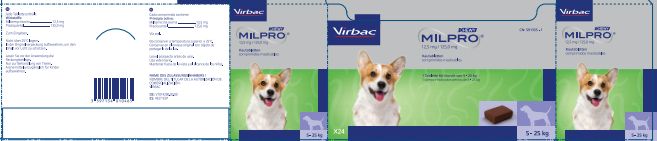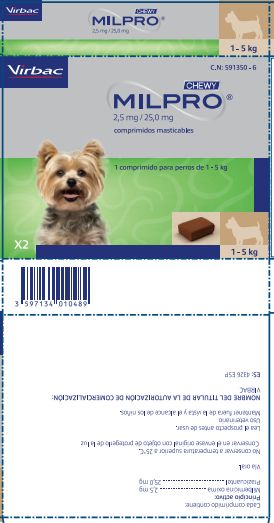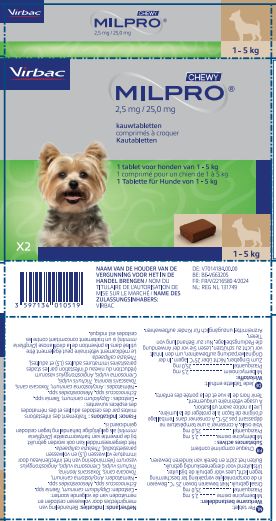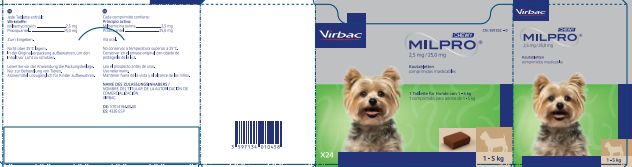 DRUG LABEL: MILPRO CHEWY
NDC: 51311-089 | Form: TABLET, CHEWABLE
Manufacturer: Virbac AH Inc
Category: animal | Type: PRESCRIPTION ANIMAL DRUG LABEL
Date: 20250611

ACTIVE INGREDIENTS: MILBEMYCIN OXIME 2.5 mg/1 1; PRAZIQUANTEL 25 mg/1 1

MILPRO® CHEWY (milbemycin oxime/praziquantel)